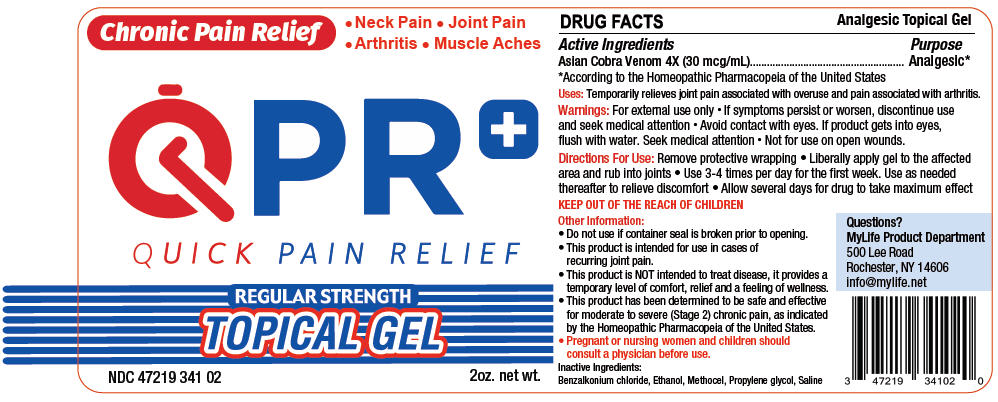 DRUG LABEL: QPR  Quick Pain Relief
NDC: 47219-341 | Form: GEL
Manufacturer: Nutra Pharma Corporation
Category: homeopathic | Type: HUMAN OTC DRUG LABEL
Date: 20160922

ACTIVE INGREDIENTS: Naja Naja Venom 4 [hp_X]/1 mL
INACTIVE INGREDIENTS: Benzalkonium chloride; Alcohol; Propylene Glycol; Sodium Chloride

QPR: Quick Pain Relief

Drug Facts

Active Ingredients

Asian Cobra Venom 4X (30 mcg/mL)

Purpose

Analgesic [According to the Homeopathic Pharmacopeia of the United States]

Uses

Temporarily relieves joint pain associated with overuse and pain associated with arthritis.

Warnings

For external use only

- If symptoms persist or worsen, discontinue use and seek medical attention
- Avoid contact with eyes. If product gets into eyes, flush with water. Seek medical attention
- Not for use on open wounds.

Directions For Use

Remove protective wrapping

- Liberally apply gel to the affected area and rub into joints
- Use 3-4 times per day for the first week. Use as needed thereafter to relieve discomfort
- Allow several days for drug to take maximum effect

KEEP OUT OF THE REACH OF CHILDREN

Other Information

- Do not use if container seal is broken prior to opening.
- This product is intended for use in cases of recurring joint pain.
- This product is NOT intended to treat disease, it provides a temporary level of comfort, relief and a feeling of wellness.
- This product has been determined to be safe and effective for moderate to severe (Stage 2) chronic pain, as indicated by the Homeopathic Pharmacopeia of the United States.
- Pregnant or nursing women and children should consult a physician before use.

Inactive Ingredients

Benzalkonium chloride, Ethanol, Methocel, Propylene glycol, Saline

Questions?

MyLife Product Department
500 Lee Road
Rochester, NY 14606
info@mylife.net

PRINCIPAL DISPLAY PANEL - 60 mL Bottle Label

Chronic Pain Relief

• Neck Pain • Joint Pain
• Arthritis • Muscle Aches

QPR^+

QUICK PAIN RELIEF

REGULAR STRENGTH
TOPICAL GEL

NDC 47219 341 02

2oz. net wt.